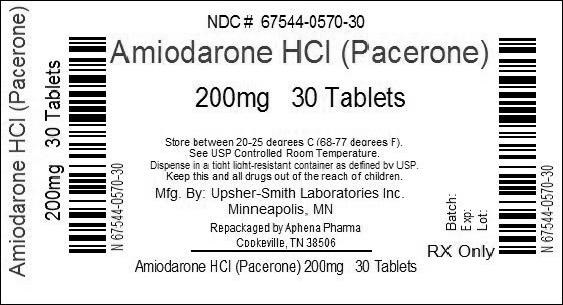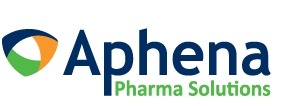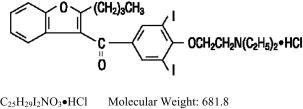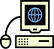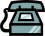 DRUG LABEL: Pacerone
NDC: 67544-570 | Form: TABLET
Manufacturer: Aphena Pharma Solutions - Tennessee, LLC
Category: prescription | Type: HUMAN PRESCRIPTION DRUG LABEL
Date: 20191223

ACTIVE INGREDIENTS: Amiodarone Hydrochloride 200 mg/1 1
INACTIVE INGREDIENTS: lactose monohydrate; magnesium stearate; povidone, unspecified; starch, corn; sodium starch glycolate type a potato; stearic acid; FD&C Red No. 40; FD&C Yellow No. 6

PACERONE®
(Amiodarone HCl) Tablets, 100 mg and 200 mg

Rx only

DESCRIPTION

Pacerone®(Amiodarone HCl) Tablets are a member of a class of antiarrhythmic drugs with predominantly Class III (Vaughan Williams' classification) effects, available for oral administration in 100 mg and 200 mg strengths of amiodarone hydrochloride. Both strengths of Pacerone® Tablets contain the following inactive ingredients: lactose monohydrate, magnesium stearate, povidone, pregelatinized corn starch, sodium starch glycolate, stearic acid, FD&C Red 40 (200 mg only) and FD&C Yellow 6.

Amiodarone hydrochloride, the active ingredient in Pacerone® Tablets, is a benzofuran derivative: 2-butyl-3-benzofuranyl 4-[2-(diethylamino)-ethoxy]-3,5-diiodophenyl ketone hydrochloride.

The structural formula is as follows:

Amiodarone HCl is a white to cream-colored crystalline powder. It is slightly soluble in water, soluble in alcohol and freely soluble in chloroform. It contains 37.3% iodine by weight.

CLINICAL PHARMACOLOGY

Electrophysiology/Mechanisms of Action

In animals, amiodarone HCl is effective in the prevention or suppression of experimentally induced arrhythmias. The antiarrhythmic effect of amiodarone may be due to at least two major properties:

1. a prolongation of the myocardial cell-action potential duration and refractory period and
2. noncompetitive α- and β -adrenergic inhibition.

Amiodarone prolongs the duration of the action potential of all cardiac fibers while causing minimal reduction of dV/dt (maximal upstroke velocity of the action potential). The refractory period is prolonged in all cardiac tissues. Amiodarone increases the cardiac refractory period without influencing resting membrane potential, except in automatic cells where the slope of the prepotential is reduced, generally reducing automaticity. These electrophysiologic effects are reflected in a decreased sinus rate of 15 to 20%, increased PR and QT intervals of about 10%, the development of U-waves and changes in T-wave contour. These changes should not require discontinuation of Pacerone® Tablets as they are evidence of its pharmacological action, although amiodarone can cause marked sinus bradycardia or sinus arrest and heart block. On rare occasions, QT prolongation has been associated with worsening of arrhythmia (see "WARNINGS").

Hemodynamics

In animal studies and after intravenous administration in man, amiodarone relaxes vascular smooth muscle, reduces peripheral vascular resistance (afterload), and slightly increases cardiac index. After oral dosing, however, amiodarone produces no significant change in left ventricular ejection fraction (LVEF), even in patients with depressed LVEF. After acute intravenous dosing in man, amiodarone may have a mild negative inotropic effect.

Pharmacokinetics

Following oral administration in man, amiodarone is slowly and variably absorbed. The bioavailability of amiodarone is approximately 50%, but has varied between 35 and 65% in various studies. Maximum plasma concentrations are attained 3 to 7 hours after a single dose. Despite this, the onset of action may occur in 2 to 3 days, but more commonly takes 1 to 3 weeks, even with loading doses. Plasma concentrations with chronic dosing at 100 to 600 mg/day are approximately dose proportional, with a mean 0.5 mg/L increase for each 100 mg/day. These means, however, include considerable individual variability. Food increases the rate and extent of absorption of amiodarone. The effects of food upon the bioavailability of amiodarone have been studied in 30 healthy subjects who received a single 600-mg dose immediately after consuming a high-fat meal and following an overnight fast. The area under the plasma concentration-time curve (AUC) and the peak plasma concentration (Cmax) of amiodarone increased by 2.3 (range 1.7 to 3.6) and 3.8 (range 2.7 to 4.4) times, respectively, in the presence of food. Food also increased the rate of absorption of amiodarone, decreasing the time to peak plasma concentration (Tmax) by 37%. The mean AUC and mean Cmax of desethylamiodarone increased by 55% (range 58 to 101%) and 32% (range 4 to 84%), respectively, but there was no change in the Tmax in the presence of food.

Amiodarone has a very large but variable volume of distribution, averaging about 60 L/kg, because of extensive accumulation in various sites, especially adipose tissue and highly perfused organs, such as the liver, lung and spleen. One major metabolite of amiodarone, desethylamiodarone (DEA), has been identified in man; it accumulates to an even greater extent in almost all tissues. No data are available on the activity of DEA in humans, but in animals, it has significant electrophysiologic and antiarrhythmic effects generally similar to amiodarone itself. DEA's precise role and contribution to the antiarrhythmic activity of oral amiodarone are not certain. The development of maximal ventricular Class III effects after oral amiodarone administration in humans correlates more closely with DEA accumulation over time than with amiodarone accumulation.

Amiodarone is metabolized to desethylamiodarone by the cytochrome P450 (CYP450) enzyme group, specifically cytochrome P450 3A4 (CYP3A4) and CYP2C8. The CYP3A4 isoenzyme is present in both the liver and intestines.

Amiodarone is eliminated primarily by hepatic metabolism and biliary excretion and there is negligible excretion of amiodarone or DEA in urine. Neither amiodarone nor DEA is dialyzable.

In clinical studies of 2 to 7 days, clearance of amiodarone after intravenous administration in patients with VT and VF ranged between 220 and 440 mL/hr/kg. Age, sex, renal disease and hepatic disease (cirrhosis) do not have marked effects on the disposition of amiodarone or DEA. Renal impairment does not influence the pharmacokinetics of amiodarone. After a single dose of intravenous amiodarone in cirrhotic patients, significantly lower Cmax and average concentration values are seen for DEA, but mean amiodarone levels are unchanged. Normal subjects over 65 years of age show lower clearances (about 100 mL/hr/kg) than younger subjects (about 150 mL/hr/kg) and an increase in t½ from about 20 to 47 days. In patients with severe left ventricular dysfunction, the pharmacokinetics of amiodarone are not significantly altered but the terminal disposition t½ of DEA is prolonged. Although no dosage adjustment for patients with renal, hepatic or cardiac abnormalities has been defined during chronic treatment with amiodarone, close clinical monitoring is prudent for elderly patients and those with severe left ventricular dysfunction.

Following single dose administration in 12 healthy subjects, amiodarone exhibited multi-compartmental pharmacokinetics with a mean apparent plasma terminal elimination half-life of 58 days (range 15 to 142 days) for amiodarone and 36 days (range 14 to 75 days) for the active metabolite (DEA). In patients, following discontinuation of chronic oral therapy, amiodarone has been shown to have a biphasic elimination with an initial one-half reduction of plasma levels after 2.5 to 10 days. A much slower terminal plasma-elimination phase shows a half-life of the parent compound ranging from 26 to 107 days, with a mean of approximately 53 days and most patients in the 40- to 55-day range. In the absence of a loading-dose period, steady-state plasma concentrations, at constant oral dosing, would therefore be reached between 130 and 535 days, with an average of 265 days. For the metabolite, the mean plasma-elimination half-life was approximately 61 days. These data probably reflect an initial elimination of drug from well-perfused tissue (the 2.5- to 10-day half-life phase), followed by a terminal phase representing extremely slow elimination from poorly perfused tissue compartments such as fat.

The considerable intersubject variation in both phases of elimination, as well as uncertainty as to what compartment is critical to drug effect, requires attention to individual responses once arrhythmia control is achieved with loading doses because the correct maintenance dose is determined, in part, by the elimination rates. Daily maintenance doses of Pacerone® Tablets should be based on individual patient requirements (see "DOSAGE AND ADMINISTRATION").

Amiodarone and its metabolite have a limited transplacental transfer of approximately 10 to 50%. The parent drug and its metabolite have been detected in breast milk.

Amiodarone is highly protein-bound (approximately 96%).

Although electrophysiologic effects, such as prolongation of QTc, can be seen within hours after a parenteral dose of amiodarone, effects on abnormal rhythms are not seen before 2 to 3 days and usually require 1 to 3 weeks, even when a loading dose is used. There may be a continued increase in effect for longer periods still. There is evidence that the time to effect is shorter when a loading-dose regimen is used.

Consistent with the slow rate of elimination, antiarrhythmic effects persist for weeks or months after Pacerone® Tablets are discontinued, but the time of recurrence is variable and unpredictable. In general, when the drug is resumed after recurrence of the arrhythmia, control is established relatively rapidly compared to the initial response, presumably because tissue stores were not wholly depleted at the time of recurrence.

Pharmacodynamics

There is no well-established relationship of plasma concentration to effectiveness, but it does appear that concentrations much below 1 mg/L are often ineffective and that levels above 2.5 mg/L are generally not needed. Within individuals, dose reductions and ensuing decreased plasma concentrations can result in loss of arrhythmia control. Plasma-concentration measurements can be used to identify patients whose levels are unusually low, and who might benefit from a dose increase, or unusually high, and who might have dosage reduction in the hope of minimizing side effects. Some observations have suggested a plasma concentration, dose or dose/duration relationship for side effects such as pulmonary fibrosis, liver-enzyme elevations, corneal deposits and facial pigmentation, peripheral neuropathy, gastrointestinal and central nervous system effects.

Monitoring Effectiveness

Predicting the effectiveness of any antiarrhythmic agent in long-term prevention of recurrent ventricular tachycardia and ventricular fibrillation is difficult and controversial, with highly qualified investigators recommending use of ambulatory monitoring, programmed electrical stimulation with various stimulation regimens, or a combination of these, to assess response. There is no present consensus on many aspects of how best to assess effectiveness, but there is a reasonable consensus on some aspects:

1. If a patient with a history of cardiac arrest does not manifest a hemodynamically unstable arrhythmia during electrocardiographic monitoring prior to treatment, assessment of the effectiveness of amiodarone requires some provocative approach, either exercise or programmed electrical stimulation (PES).
2. Whether provocation is also needed in patients who do manifest their life-threatening arrhythmia spontaneously is not settled, but there are reasons to consider PES or other provocation in such patients. In the fraction of patients whose PES-inducible arrhythmia can be made noninducible by amiodarone (a fraction that has varied widely in various series from less than 10% to almost 40%, perhaps due to different stimulation criteria), the prognosis has been almost uniformly excellent, with very low recurrence (ventricular tachycardia or sudden death) rates. More controversial is the meaning of continued inducibility. There has been an impression that continued inducibility in amiodarone patients may not foretell a poor prognosis but, in fact, many observers have found greater recurrence rates in patients who remain inducible than in those who do not. A number of criteria have been proposed, however, for identifying patients who remain inducible but who seem likely nonetheless to do well on Pacerone® Tablets. These criteria include increased difficulty of induction (more stimuli or more rapid stimuli), which has been reported to predict a lower rate of recurrence, and ability to tolerate the induced ventricular tachycardia without severe symptoms, a finding that has been reported to correlate with better survival but not with lower recurrence rates. While these criteria require confirmation and further study in general, easier inducibility or poorer tolerance of the induced arrhythmia should suggest consideration of a need to revise treatment.

Several predictors of success not based on PES have also been suggested, including complete elimination of all nonsustained ventricular tachycardia on ambulatory monitoring and very low premature ventricular-beat rates (less than 1 VPB/1,000 normal beats).

While these issues remain unsettled for amiodarone, as for other agents, the prescriber of Pacerone® Tablets should have access to (direct or through referral), and familiarity with, the full range of evaluatory procedures used in the care of patients with life-threatening arrhythmias.

It is difficult to describe the effectiveness rates of Pacerone® Tablets, as these depend on the specific arrhythmia treated, the success criteria used, the underlying cardiac disease of the patient, the number of drugs tried before resorting to Pacerone® Tablets, the duration of follow-up, the dose of amiodarone HCl, the use of additional antiarrhythmic agents and many other factors. As amiodarone has been studied principally in patients with refractory life-threatening ventricular arrhythmias, in whom drug therapy must be selected on the basis of response and cannot be assigned arbitrarily, randomized comparisons with other agents or placebo have not been possible. Reports of series of treated patients with a history of cardiac arrest and mean follow-up of one year or more have given mortality (due to arrhythmia) rates that were highly variable, ranging from less than 5% to over 30%, with most series in the range of 10 to 15%. Overall arrhythmia-recurrence rates (fatal and nonfatal) also were highly variable (and, as noted above, depended on response to PES and other measures), and depend on whether patients who do not seem to respond initially are included. In most cases, considering only patients who seemed to respond well enough to be placed on long-term treatment, recurrence rates have ranged from 20 to 40% in series with a mean follow-up of a year or more.

INDICATIONS AND USAGE

Because of its life-threatening side effects and the substantial management difficulties associated with amiodarone use (see "WARNINGS" below), Pacerone® (Amiodarone HCl) Tablets are indicated only for the treatment of the following documented, life-threatening recurrent ventricular arrhythmias when these have not responded to documented adequate doses of other available antiarrhythmics or when alternative agents could not be tolerated.

1. Recurrent ventricular fibrillation.
2. Recurrent hemodynamically unstable ventricular tachycardia.

As is the case for other antiarrhythmic agents, there is no evidence from controlled trials that the use of amiodarone HCl tablets favorably affects survival.

Pacerone® (Amiodarone HCl) Tablets should be used only by physicians familiar with and with access to (directly or through referral) the use of all available modalities for treating recurrent life-threatening ventricular arrhythmias, and who have access to appropriate monitoring facilities, including in-hospital and ambulatory continuous electrocardiographic monitoring and electrophysiologic techniques. Because of the life-threatening nature of the arrhythmias treated, potential interactions with prior therapy and potential exacerbation of the arrhythmia, initiation of therapy with Pacerone® (Amiodarone HCl) Tablets should be carried out in the hospital.

CONTRAINDICATIONS

Pacerone® (Amiodarone HCl) Tablets are contraindicated in patients with cardiogenic shock; severe sinus-node dysfunction, causing marked sinus bradycardia; second- or third-degree atrioventricular block; and when episodes of bradycardia have caused syncope (except when used in conjunction with a pacemaker).

Pacerone® (Amiodarone HCl) Tablets are contraindicated in patients with a known hypersensitivity to the drug or to any of its components, including iodine.

WARNINGS

BOXED WARNING

Pacerone® (Amiodarone HCl) Tablets are intended for use only in patients with the indicated life-threatening arrhythmias because amiodarone use is accompanied by substantial toxicity.

Amiodarone has several potentially fatal toxicities, the most important of which is pulmonary toxicity (hypersensitivity pneumonitis or interstitial/alveolar pneumonitis) that has resulted in clinically manifest disease at rates as high as 10 to 17% in some series of patients with ventricular arrhythmias given doses around 400 mg/day, and as abnormal diffusion capacity without symptoms in a much higher percentage of patients. Pulmonary toxicity has been fatal about 10% of the time. Liver injury is common with amiodarone, but is usually mild and evidenced only by abnormal liver enzymes. Overt liver disease can occur, however, and has been fatal in a few cases. Like other antiarrhythmics, amiodarone can exacerbate the arrhythmia, e.g., by making the arrhythmia less well tolerated or more difficult to reverse. This has occurred in 2 to 5% of patients in various series, and significant heart block or sinus bradycardia has been seen in 2 to 5%. All of these events should be manageable in the proper clinical setting in most cases. Although the frequency of such proarrhythmic events does not appear greater with amiodarone than with many other agents used in this population, the effects are prolonged when they occur.

Even in patients at high risk of arrhythmic death, in whom the toxicity of amiodarone is an acceptable risk, Pacerone® Tablets pose major management problems that could be life-threatening in a population at risk of sudden death, so that every effort should be made to utilize alternative agents first.

The difficulty of using Pacerone® Tablets effectively and safely itself poses a significant risk to patients. Patients with the indicated arrhythmias must be hospitalized while the loading dose of Pacerone® Tablets is given, and a response generally requires at least one week, usually two or more. Because absorption and elimination are variable, maintenance-dose selection is difficult, and it is not unusual to require dosage decrease or discontinuation of treatment. In a retrospective survey of 192 patients with ventricular tachyarrhythmias, 84 required dose reduction and 18 required at least temporary discontinuation because of adverse effects, and several series have reported 15 to 20% overall frequencies of discontinuation due to adverse reactions. The time at which a previously controlled life-threatening arrhythmia will recur after discontinuation or dose adjustment is unpredictable, ranging from weeks to months. The patient is obviously at great risk during this time and may need prolonged hospitalization. Attempts to substitute other antiarrhythmic agents when Pacerone® Tablets must be stopped will be made difficult by the gradually, but unpredictably, changing amiodarone body burden. A similar problem exists when amiodarone is not effective; it still poses the risk of an interaction with whatever subsequent treatment is tried.

Mortality

In the National Heart, Lung and Blood Institute's Cardiac Arrhythmia Suppression Trial (CAST), a long-term, multi-centered, randomized, double-blind study in patients with asymptomatic non-life-threatening ventricular arrhythmias who had had myocardial infarctions more than six days but less than two years previously, an excessive mortality or non-fatal cardiac arrest rate was seen in patients treated with encainide or flecainide (56/730) compared with that seen in patients assigned to matched placebo-treated groups (22/725). The average duration of treatment with encainide or flecainide in this study was ten months.

Amiodarone therapy was evaluated in two multi-centered, randomized, double-blind, placebo-controlled trials involving 1202 (Canadian Amiodarone Myocardial Infarction Arrhythmia Trial; CAMIAT) and 1486 (European Myocardial Infarction Amiodarone Trial; EMIAT) post-MI patients followed for up to 2 years. Patients in CAMIAT qualified with ventricular arrhythmias, and those randomized to amiodarone received weight- and response-adjusted doses of 200 to 400 mg/day. Patients in EMIAT qualified with ejection fraction <40%, and those randomized to amiodarone received fixed doses of 200 mg/day. Both studies had weeks-long loading dose schedules. Intent-to-treat all-cause mortality results were as follows:

 | Placebo |  | Amiodarone |  | Relative Risk
 | N | Deaths | N | Deaths |  | 95% CI
EMIAT | 743 | 102 | 743 | 103 | 0.99 | 0.76-1.31
CAMIAT | 596 | 68 | 606 | 57 | 0.88 | 0.58-1.16

These data are consistent with the results of a pooled analysis of smaller, controlled studies involving patients with structural heart disease (including myocardial infarction).

Pulmonary Toxicity

There have been post-marketing reports of acute-onset (days to weeks) pulmonary injury in patients treated with oral amiodarone with or without initial I.V. therapy. Findings have included pulmonary infiltrates and/or mass on X-ray, pulmonary alveolar hemorrhage, pleural effusion, bronchospasm, wheezing, fever, dyspnea, cough, hemoptysis, and hypoxia. Some cases have progressed to respiratory failure and/or death. Post-marketing reports describe cases of pulmonary toxicity in patients treated with low doses of amiodarone; however, reports suggest that the use of lower loading and maintenance doses of amiodarone are associated with a decreased incidence of amiodarone-induced pulmonary toxicity.

Amiodarone HCl Tablets may cause a clinical syndrome of cough and progressive dyspnea accompanied by functional, radiographic, gallium-scan, and pathological data consistent with pulmonary toxicity, the frequency of which varies from 2 to 7% in most published reports, but is as high as 10 to 17% in some reports. Therefore, when Pacerone® Tablets therapy is initiated, a baseline chest X-ray and pulmonary-function tests, including diffusion capacity, should be performed. The patient should return for a history, physical exam and chest X-ray every 3 to 6 months.

Pulmonary toxicity secondary to amiodarone seems to result from either indirect or direct toxicity as represented by hypersensitivity pneumonitis (including eosinophilic pneumonia) or interstitial/alveolar pneumonitis, respectively.

Patients with preexisting pulmonary disease have a poorer prognosis if pulmonary toxicity develops.

Hypersensitivity pneumonitis usually appears earlier in the course of therapy and rechallenging these patients with Pacerone® Tablets results in a more rapid recurrence of greater severity.

Bronchoalveolar lavage is the procedure of choice to confirm this diagnosis, which can be made when a T suppressor/cytotoxic (CD8-positive) lymphocytosis is noted. Steroid therapy should be instituted and Pacerone® Tablets therapy discontinued in these patients.

Interstitial/alveolar pneumonitis may result from the release of oxygen radicals and/or phospholipidosis and is characterized by findings of diffuse alveolar damage, interstitial pneumonitis or fibrosis in lung biopsy specimens. Phospholipidosis (foamy cells, foamy macrophages), due to inhibition of phospholipase, will be present in most cases of amiodarone-induced pulmonary toxicity; however, these changes also are present in approximately 50% of all patients on amiodarone therapy. These cells should be used as markers of therapy, but not as evidence of toxicity. A diagnosis of amiodarone-induced interstitial/alveolar pneumonitis should lead, at a minimum, to dose reduction or, preferably, to withdrawal of Pacerone® Tablets to establish reversibility, especially if other acceptable antiarrhythmic therapies are available. Where these measures have been instituted, a reduction in symptoms of amiodarone-induced pulmonary toxicity was usually noted within the first week, and a clinical improvement was greatest in the first two to three weeks. Chest X-ray changes usually resolve within two to four months. According to some experts, steroids may prove beneficial. Prednisone in doses of 40 to 60 mg/day or equivalent doses of other steroids have been given and tapered over the course of several weeks depending upon the condition of the patient. In some cases rechallenge with amiodarone at a lower dose has not resulted in return of toxicity.

In a patient receiving Pacerone® Tablets, any new respiratory symptoms should suggest the possibility of pulmonary toxicity, and the history, physical exam, chest X-ray and pulmonary-function tests (with diffusion capacity) should be repeated and evaluated. A 15% decrease in diffusion capacity has a high sensitivity but only a moderate specificity for pulmonary toxicity; as the decrease in diffusion capacity approaches 30%, the sensitivity decreases but the specificity increases. A gallium-scan also may be performed as part of the diagnostic workup.

Fatalities, secondary to pulmonary toxicity, have occurred in approximately 10% of cases. However, in patients with life-threatening arrhythmias, discontinuation of Pacerone® Tablets therapy due to suspected drug-induced pulmonary toxicity should be undertaken with caution, as the most common cause of death in these patients is sudden cardiac death. Therefore, every effort should be made to rule out other causes of respiratory impairment (i.e., congestive heart failure with Swan-Ganz catheterization if necessary, respiratory infection, pulmonary embolism, malignancy, etc.) before discontinuing Pacerone® Tablets in these patients. In addition, bronchoalveolar lavage, transbronchial lung biopsy and/or open lung biopsy may be necessary to confirm the diagnosis, especially in those cases where no acceptable alternative therapy is available.

If a diagnosis of amiodarone-induced hypersensitivity pneumonitis is made, Pacerone® Tablets should be discontinued, and treatment with steroids should be instituted. If a diagnosis of amiodarone-induced interstitial/alveolar pneumonitis is made, steroid therapy should be instituted and, preferably, Pacerone® Tablets discontinued or, at a minimum, reduced in dosage. Some cases of amiodarone-induced interstitial/alveolar pneumonitis may resolve following a reduction in Pacerone® Tablets dosage in conjunction with the administration of steroids. In some patients, rechallenge at a lower dose has not resulted in return of interstitial/alveolar pneumonitis; however, in some patients (perhaps because of severe alveolar damage) the pulmonary lesions have not been reversible.

Worsened Arrhythmia

Amiodarone, like other antiarrhythmics, can cause serious exacerbation of the presenting arrhythmia, a risk that may be enhanced by the presence of concomitant antiarrhythmics. Exacerbation has been reported in about 2 to 5% in most series, and has included new ventricular fibrillation, incessant ventricular tachycardia, increased resistance to cardioversion and polymorphic ventricular tachycardia associated with QTc prolongation (Torsade de Pointes [TdP]). In addition, amiodarone has caused symptomatic bradycardia or sinus arrest with suppression of escape foci in 2 to 4% of patients.

Fluoroquinolones, macrolide antibiotics, and azoles are known to cause QTc prolongation. There have been reports of QTc prolongation, with or without TdP, in patients taking amiodarone when fluoroquinolones, macrolide antibiotics, or azoles were administered concomitantly. (See "Drug Interactions, Other reported interactions with amiodarone".)

The need to co-administer amiodarone with any other drug known to prolong the QTc interval must be based on a careful assessment of the potential risks and benefits of doing so for each patient.

A careful assessment of the potential risks and benefits of administering Pacerone® Tablets must be made in patients with thyroid dysfunction due to the possibility of arrhythmia breakthrough or exacerbation of arrhythmia in these patients.

Implantable Cardiac Devices

In patients with implanted defibrillators or pacemakers, chronic administration of antiarrhythmic drugs may affect pacing or defibrillating thresholds. Therefore, at the inception of and during amiodarone treatment, pacing and defibrillation thresholds should be assessed.

Thyrotoxicosis

Amiodarone-induced hyperthyroidism may result in thyrotoxicosis and/or the possibility of arrhythmia breakthrough or aggravation. There have been reports of death associated with amiodarone-induced thyrotoxicosis. IF ANY NEW SIGNS OF ARRHYTHMIA APPEAR, THE POSSIBILITY OF HYPERTHYROIDISM SHOULD BE CONSIDERED (see "PRECAUTIONS, Thyroid Abnormalities").

Liver Injury

Elevations of hepatic enzyme levels are seen frequently in patients exposed to amiodarone and in most cases are asymptomatic. If the increase exceeds three times normal, or doubles in a patient with an elevated baseline, discontinuation of Pacerone® Tablets or dosage reduction should be considered. In a few cases in which biopsy has been done, the histology has resembled that of alcoholic hepatitis or cirrhosis. Hepatic failure has been a rare cause of death in patients treated with amiodarone.

Loss of Vision

Cases of optic neuropathy and/or optic neuritis, usually resulting in visual impairment, have been reported in patients treated with amiodarone. In some cases, visual impairment has progressed to permanent blindness. Optic neuropathy and/or neuritis may occur at any time following initiation of therapy. A causal relationship to the drug has not been clearly established. If symptoms of visual impairment appear, such as changes in visual acuity and decreases in peripheral vision, prompt ophthalmic examination is recommended. Appearance of optic neuropathy and/or neuritis calls for re-evaluation of Pacerone® Tablets therapy. The risks and complications of antiarrhythmic therapy with Pacerone® Tablets must be weighed against its benefits in patients whose lives are threatened by cardiac arrhythmias. Regular ophthalmic examination, including funduscopy and slit-lamp examination, is recommended during administration of Pacerone® Tablets (see "ADVERSE REACTIONS").

Neonatal Hypo- or Hyperthyroidism

Amiodarone can cause fetal harm when administered to a pregnant woman. Although amiodarone use during pregnancy is uncommon, there have been a small number of published reports of congenital goiter/hypothyroidism and hyperthyroidism. If Pacerone® (Amiodarone HCl) Tablets are used during pregnancy, or if the patient becomes pregnant while taking Pacerone® Tablets, the patient should be apprised of the potential hazard to the fetus.

In general, Pacerone® Tablets should be used during pregnancy only if the potential benefit to the mother justifies the unknown risk to the fetus.

In pregnant rats and rabbits, amiodarone HCl in doses of 25 mg/kg/day (approximately 0.4 and 0.9 times, respectively, the maximum recommended human maintenance dose*) had no adverse effects on the fetus. In the rabbit, 75 mg/kg/day (approximately 2.7 times the maximum recommended human maintenance dose*) caused abortions in greater than 90% of the animals. In the rat, doses of 50 mg/kg/day or more were associated with slight displacement of the testes and an increased incidence of incomplete ossification of some skull and digital bones; at 100 mg/kg/day or more, fetal body weights were reduced; at 200 mg/kg/day, there was an increased incidence of fetal resorption. (These doses in the rat are approximately 0.8, 1.6 and 3.2 times the maximum recommended human maintenance dose.*) Adverse effects on fetal growth and survival also were noted in one of two strains of mice at a dose of 5 mg/kg/day (approximately 0.04 times the maximum recommended human maintenance dose*).

*600 mg in a 50 kg patient (doses compared on a body surface area basis)

PRECAUTIONS

Impairment of Vision

Optic Neuropathy and/or Neuritis

Cases of optic neuropathy and optic neuritis have been reported (see "WARNINGS").

Corneal Microdeposits

Corneal microdeposits appear in the majority of adults treated with amiodarone. They are usually discernible only by slit-lamp examination, but give rise to symptoms such as visual halos or blurred vision in as many as 10% of patients. Corneal microdeposits are reversible upon reduction of dose or termination of treatment. Asymptomatic microdeposits alone are not a reason to reduce dose or discontinue treatment (see "ADVERSE REACTIONS").

Neurologic

Chronic administration of oral amiodarone in rare instances may lead to the development of peripheral neuropathy that may resolve when amiodarone is discontinued, but this resolution has been slow and incomplete.

Photosensitivity

Amiodarone has induced photosensitization in about 10% of patients; some protection may be afforded by the use of sun-barrier creams or protective clothing. During long-term treatment, a blue-gray discoloration of the exposed skin may occur. The risk may be increased in patients of fair complexion or those with excessive sun exposure, and may be related to cumulative dose and duration of therapy.

Thyroid Abnormalities

Amiodarone inhibits peripheral conversion of thyroxine (T4) to triiodothyronine (T3) and may cause increased thyroxine levels, decreased T3 levels and increased levels of inactive reverse T3 (rT3) in clinically euthyroid patients. It is also a potential source of large amounts of inorganic iodine. Because of its release of inorganic iodine, or perhaps for other reasons, amiodarone can cause either hypothyroidism or hyperthyroidism. Thyroid function should be monitored prior to treatment and periodically thereafter, particularly in elderly patients, and in any patient with a history of thyroid nodules, goiter or other thyroid dysfunction. Because of the slow elimination of amiodarone and its metabolites, high plasma iodide levels, altered thyroid function and abnormal thyroid-function tests may persist for several weeks or even months following Pacerone® (Amiodarone HCl) Tablets withdrawal.

Hypothyroidism has been reported in 2 to 4% of patients in most series, but in 8 to 10% in some series. This condition may be identified by relevant clinical symptoms and particularly by elevated serum TSH levels. In some clinically hypothyroid amiodarone-treated patients, free thyroxine index values may be normal. Hypothyroidism is best managed by Pacerone® Tablets dose reduction and/or thyroid hormone supplement. However, therapy must be individualized, and it may be necessary to discontinue Pacerone® Tablets in some patients.

Hyperthyroidism occurs in about 2% of patients receiving amiodarone, but the incidence may be higher among patients with prior inadequate dietary iodine intake. Amiodarone-induced hyperthyroidism usually poses a greater hazard to the patient than hypothyroidism because of the possibility of thyrotoxicosis and/or arrhythmia breakthrough or aggravation, all of which may result in death. There have been reports of death associated with amiodarone-induced thyrotoxicosis. IF ANY NEW SIGNS OF ARRHYTHMIA APPEAR, THE POSSIBILITY OF HYPERTHYROIDISM SHOULD BE CONSIDERED.

Hyperthyroidism is best identified by relevant clinical symptoms and signs, accompanied usually by abnormally elevated levels of serum T3 RIA, and further elevations of serum T4, and a subnormal serum TSH level (using a sufficiently sensitive TSH assay). The finding of a flat TSH response to TRH is confirmatory of hyperthyroidism and may be sought in equivocal cases. Since arrhythmia breakthroughs may accompany amiodarone-induced hyperthyroidism, aggressive medical treatment is indicated, including, if possible, dose reduction or withdrawal of Pacerone® Tablets.

The institution of antithyroid drugs, β-adrenergic blockers and/or temporary corticosteroid therapy may be necessary. The action of antithyroid drugs may be especially delayed in amiodarone-induced thyrotoxicosis because of substantial quantities of preformed thyroid hormones stored in the gland. Radioactive iodine therapy is contraindicated because of the low radioiodine uptake associated with amiodarone-induced hyperthyroidism. Amiodarone-induced hyperthyroidism may be followed by a transient period of hypothyroidism (see "WARNINGS, Thyrotoxicosis").

When aggressive treatment of amiodarone-induced thyrotoxicosis has failed or amiodarone cannot be discontinued because it is the only drug effective against the resistant arrhythmia, surgical management may be an option. Experience with thyroidectomy as a treatment for amiodarone-induced thyrotoxicosis is limited, and this form of therapy could induce thyroid storm. Therefore, surgical and anesthetic management require careful planning.

There have been postmarketing reports of thyroid nodules/thyroid cancer in patients treated with amiodarone. In some instances hyperthyroidism was also present (see "WARNINGS" and "ADVERSE REACTIONS").

Surgery

Volatile Anesthetic Agents: Close perioperative monitoring is recommended in patients undergoing general anesthesia who are on amiodarone therapy as they may be more sensitive to the myocardial depressant and conduction effects of halogenated inhalational anesthetics.

Hypotension Postbypass: Rare occurrences of hypotension upon discontinuation of cardiopulmonary bypass during open-heart surgery in patients receiving amiodarone have been reported. The relationship of this event to Pacerone® Tablets therapy is unknown.

Adult Respiratory Distress Syndrome (ARDS): Postoperatively, occurrences of ARDS have been reported in patients receiving amiodarone therapy who have undergone either cardiac or noncardiac surgery. Although patients usually respond well to vigorous respiratory therapy, in rare instances the outcome has been fatal. Until further studies have been performed, it is recommended that FiO2 and the determinants of oxygen delivery to the tissues (e.g., SaO2, PaO2) be closely monitored in patients on amiodarone.

Corneal Refractive Laser Surgery

Patients should be advised that most manufacturers of corneal refractive laser surgery devices contraindicate that procedure in patients taking amiodarone.

Information for Patients

Patients should be instructed to read the accompanying Medication Guide each time they refill their prescription. The complete text of the Medication Guide is reprinted at the end of this document.

Laboratory Tests

Elevations in liver enzymes (SGOT and SGPT) can occur. Liver enzymes in patients on relatively high maintenance doses should be monitored on a regular basis. Persistent significant elevations in the liver enzymes or hepatomegaly should alert the physician to consider reducing the maintenance dose of Pacerone® Tablets or discontinuing therapy.

Amiodarone alters the results of thyroid-function tests, causing an increase in serum T4 and serum reverse T3, and a decline in serum T3 levels. Despite these biochemical changes, most patients remain clinically euthyroid.

Drug Interactions

Amiodarone is metabolized to desethylamiodarone by the cytochrome P450 (CYP450) enzyme group, specifically cytochrome P450 3A4 (CYP3A4) and CYP2C8. The CYP3A4 isoenzyme is present in both the liver and intestines (see "CLINICAL PHARMACOLOGY, Pharmacokinetics"). Amiodarone is an inhibitor of CYP3A4 and p-glycoprotein. Therefore, amiodarone has the potential for interactions with drugs or substances that may be substrates, inhibitors or inducers of CYP3A4 and substrates of p-glycoprotein. While only a limited number of in vivo drug-drug interactions with amiodarone have been reported, the potential for other interactions should be anticipated. This is especially important for drugs associated with serious toxicity, such as other antiarrhythmics. If such drugs are needed, their dose should be reassessed and, where appropriate, plasma concentration measured. In view of the long and variable half-life of amiodarone, potential for drug interactions exists, not only with concomitant medication, but also with drugs administered after discontinuation of amiodarone.

Since amiodarone is a substrate for CYP3A4 and CYP2C8, drugs/substances that inhibit CYP3A4 may decrease the metabolism and increase serum concentrations of amiodarone. Reported examples include the following:

Protease inhibitors:

Protease inhibitors are known to inhibit CYP3A4 to varying degrees. A case report of one patient taking amiodarone 200 mg and indinavir 800 mg three times a day resulted in increases in amiodarone concentrations from 0.9 mg/L to 1.3 mg/L. DEA concentrations were not affected. There was no evidence of toxicity. Monitoring for amiodarone toxicity and serial measurement of amiodarone serum concentration during concomitant protease inhibitor therapy should be considered.

Histamine H1 antagonists:

Loratadine, a non-sedating antihistaminic, is metabolized primarily by CYP3A4. QT interval prolongation and Torsade de Pointes have been reported with the co-administration of loratadine and amiodarone.

Histamine H2 antagonists:

Cimetidine inhibits CYP3A4 and can increase serum amiodarone levels.

Antidepressants:

Trazodone, an antidepressant, is metabolized primarily by CYP3A4. QT interval prolongation and Torsade de Pointes have been reported with the co-administration of trazodone and amiodarone.

Other substances:

Grapefruit juice given to healthy volunteers increased amiodarone AUC by 50% and Cmax by 84%, and decreased DEA to unquantifiable concentrations. Grapefruit juice inhibits CYP3A4-mediated metabolism of oral amiodarone in the intestinal mucosa, resulting in increased plasma levels of amiodarone; therefore, grapefruit juice should not be taken during treatment with oral amiodarone. This information should be considered when changing from intravenous amiodarone to oral amiodarone (see "DOSAGE AND ADMINISTRATION").

Amiodarone inhibits p-glycoprotein and certain CYP450 enzymes, including CYP1A2, CYP2C9, CYP2D6, and CYP3A4. This inhibition can result in unexpectedly high plasma levels of other drugs which are metabolized by those CYP450 enzymes or are substrates of p-glycoprotein. Reported examples of this interaction include the following:

Immunosuppressives:

Cyclosporine (CYP3A4 substrate) administered in combination with oral amiodarone has been reported to produce persistently elevated plasma concentrations of cyclosporine resulting in elevated creatinine, despite reduction in dose of cyclosporine.

HMG-CoA Reductase Inhibitors:

The use of HMG-CoA reductase inhibitors that are CYP3A4 substrates in combination with amiodarone has been associated with reports of myopathy/rhabdomyolysis.

Limit the dose of simvastatin in patients on amiodarone to 20 mg daily. Limit the daily dose of lovastatin to 40 mg. Lower starting and maintenance doses of other CYP3A4 substrates (e.g., atorvastatin) may be required as amiodarone may increase the plasma concentration of these drugs.

Cardiovasculars:

Cardiac glycosides: In patients receiving digoxin therapy, administration of oral amiodarone regularly results in an increase in the serum digoxin concentration that may reach toxic levels with resultant clinical toxicity. Amiodarone taken concomitantly with digoxin increases the serum digoxin concentration by 70% after one day. On initiation of oral amiodarone, the need for digitalis therapy should be reviewed and the dose reduced by approximately 50% or discontinued. If digitalis treatment is continued, serum levels should be closely monitored and patients observed for clinical evidence of toxicity. These precautions probably should apply to digitoxin administration as well.

Antiarrhythmics:
Other antiarrhythmic drugs, such as quinidine, procainamide, disopyramide and phenytoin, have been used concurrently with oral amiodarone.

There have been case reports of increased steady-state levels of quinidine, procainamide and phenytoin during concomitant therapy with amiodarone. Phenytoin decreases serum amiodarone levels. Amiodarone taken concomitantly with quinidine increases quinidine serum concentration by 33% after two days. Amiodarone taken concomitantly with procainamide for less than seven days increases plasma concentrations of procainamide and n-acetyl procainamide by 55% and 33%, respectively. Quinidine and procainamide doses should be reduced by one-third when either is administered with amiodarone. Plasma levels of flecainide have been reported to increase in the presence of oral amiodarone; because of this, the dosage of flecainide should be adjusted when these drugs are administered concomitantly. In general, any added antiarrhythmic drug should be initiated at a lower than usual dose with careful monitoring.

Combination of amiodarone with other antiarrhythmic therapy should be reserved for patients with life-threatening ventricular arrhythmias who are incompletely responsive to a single agent or incompletely responsive to amiodarone. During transfer to amiodarone, the dose levels of previously administered agents should be reduced by 30 to 50% several days after the addition of amiodarone, when arrhythmia suppression should be beginning. The continued need for the other antiarrhythmic agent should be reviewed after the effects of amiodarone have been established, and discontinuation ordinarily should be attempted. If the treatment is continued, these patients should be particularly carefully monitored for adverse effects, especially conduction disturbances and exacerbation of tachyarrhythmias, as amiodarone is continued. In amiodarone-treated patients who require additional antiarrhythmic therapy, the initial dose of such agents should be approximately half of the usual recommended dose.

Antihypertensives:
Amiodarone should be used with caution in patients receiving β-receptor blocking agents (e.g., propranolol, a CYP3A4 inhibitor) or calcium channel antagonists (e.g., verapamil, a CYP3A4 substrate, and diltiazem, a CYP3A4 inhibitor) because of the possible potentiation of bradycardia, sinus arrest and AV block; if necessary, amiodarone can continue to be used after insertion of a pacemaker in patients with severe bradycardia or sinus arrest.

Anticoagulants:
Potentiation of warfarin-type (CYP2C9 and CYP3A4 substrate) anticoagulant response is almost always seen in patients receiving amiodarone and can result in serious or fatal bleeding. Since the concomitant administration of warfarin with amiodarone increases the prothrombin time by 100% after 3 to 4 days, the dose of the anticoagulant should be reduced by one-third to one-half, and prothrombin times should be monitored closely.

Clopidogrel, an inactive thienopyridine prodrug, is metabolized in the liver by CYP3A4 to an active metabolite. A potential interaction between clopidogrel and amiodarone resulting in ineffective inhibition of platelet aggregation has been reported.

Some drugs/substances are known to accelerate the metabolism of amiodarone by stimulating the synthesis of CYP3A4 (enzyme induction). This may lead to low amiodarone serum levels and potential decrease in efficacy. Reported examples of this interaction include the following:

Antibiotics:

Rifampin is a potent inducer of CYP3A4. Administration of rifampin concomitantly with oral amiodarone has been shown to result in decreases in serum concentrations of amiodarone and desethylamiodarone.

Other substances, including herbal preparations:

St. John's Wort (Hypericum perforatum) induces CYP3A4. Since amiodarone is a substrate for CYP3A4, there is the potential that the use of St. John's Wort in patients receiving amiodarone could result in reduced amiodarone levels.

Other reported interactions with amiodarone:

Fentanyl (CYP3A4 substrate) in combination with amiodarone may cause hypotension, bradycardia, and decreased cardiac output.

Sinus bradycardia has been reported with oral amiodarone in combination with lidocaine (CYP3A4 substrate) given for local anesthesia. Seizure, associated with increased lidocaine concentrations, has been reported with concomitant administration of intravenous amiodarone.

Dextromethorphan is a substrate for both CYP2D6 and CYP3A4. Amiodarone inhibits CYP2D6.

Cholestyramine increases enterohepatic elimination of amiodarone and may reduce its serum levels and t½.

Disopyramide increases QT prolongation which could cause arrhythmia.

Fluoroquinolones, macrolide antibiotics, and azoles are known to cause QTc prolongation. There have been reports of QTc prolongation, with or without TdP, in patients taking amiodarone when fluoroquinolones, macrolide antibiotics, or azoles were administered concomitantly. (See "WARNINGS, Worsened Arrhythmia".)

Hemodynamic and electrophysiologic interactions have also been observed after concomitant administration with propranolol, diltiazem and verapamil.

Volatile Anesthetic Agents (See "PRECAUTIONS, Surgery, Volatile Anesthetic Agents").

In addition to the interactions noted above, chronic (>2 weeks) oral amiodarone administration impairs metabolism of phenytoin, dextromethorphan and methotrexate.

Electrolyte Disturbances

Since antiarrhythmic drugs may be ineffective or may be arrhythmogenic in patients with hypokalemia, any potassium or magnesium deficiency should be corrected before instituting and during Pacerone® (Amiodarone HCl) Tablets therapy. Use caution when coadministering Pacerone® Tablets with drugs which may induce hypokalemia and/or hypomagnesemia.

Carcinogenesis, Mutagenesis, Impairment of Fertility

Amiodarone HCl was associated with a statistically significant, dose-related increase in the incidence of thyroid tumors (follicular adenoma and/or carcinoma) in rats. The incidence of thyroid tumors was greater than control even at the lowest dose level tested, i.e., 5 mg/kg/day (approximately 0.08 times the maximum recommended human maintenance dose*).

Mutagenicity studies (Ames, micronucleus and lysogenic tests) with amiodarone were negative.

In a study in which amiodarone HCl was administered to male and female rats, beginning 9 weeks prior to mating, reduced fertility was observed at a dose level of 90 mg/kg/day (approximately 1.4 times the maximum recommended human maintenance dose*).

*600 mg in a 50 kg patient (dose compared on a body surface area basis)

Pregnancy: Pregnancy Category D

See "WARNINGS, Neonatal Hypo- or Hyperthyroidism".

Labor and Delivery

It is not known whether the use of Pacerone® Tablets during labor or delivery has any immediate or delayed adverse effects. Preclinical studies in rodents have not shown any effect of amiodarone on the duration of gestation or on parturition.

Nursing Mothers

Amiodarone and one of its major metabolites, desethylamiodarone (DEA), are excreted in human milk, suggesting that breast-feeding could expose the nursing infant to a significant dose of the drug. Nursing offspring of lactating rats administered amiodarone have been shown to be less viable and have reduced body-weight gains. Therefore, when Pacerone® Tablets therapy is indicated, the mother should be advised to discontinue nursing.

Pediatric Use

The safety and effectiveness of Pacerone® (Amiodarone HCl) Tablets in pediatric patients have not been established.

Geriatric Use

Clinical studies of amiodarone HCl tablets did not include sufficient numbers of subjects aged 65 and over to determine whether they respond differently from younger subjects. Other reported clinical experience has not identified differences in responses between the elderly and younger patients. In general, dose selection for an elderly patient should be cautious, usually starting at the low end of the dosing range, reflecting the greater frequency of decreased hepatic, renal or cardiac function, and of concomitant disease or other drug therapy.

ADVERSE REACTIONS

Adverse reactions have been very common in virtually all series of patients treated with amiodarone HCl for ventricular arrhythmias with relatively large doses of drug (400 mg/day and above), occurring in about three-fourths of all patients and causing discontinuation in 7 to 18%. The most serious reactions are pulmonary toxicity, exacerbation of arrhythmia and rare serious liver injury (see "WARNINGS"), but other adverse effects constitute important problems. They are often reversible with dose reduction or cessation of amiodarone treatment. Most of the adverse effects appear to become more frequent with continued treatment beyond six months, although rates appear to remain relatively constant beyond one year. The time and dose relationships of adverse effects are under continued study.

Neurologic problems are extremely common, occurring in 20 to 40% of patients and including malaise and fatigue, tremor and involuntary movements, poor coordination and gait, and peripheral neuropathy; they are rarely a reason to stop therapy and may respond to dose reductions or discontinuation (see "PRECAUTIONS"). There have been spontaneous reports of demyelinating polyneuropathy.

Gastrointestinal complaints, most commonly nausea, vomiting, constipation and anorexia, occur in about 25% of patients but rarely require discontinuation of drug. These commonly occur during high-dose administration (i.e., loading dose) and usually respond to dose reduction or divided doses.

Ophthalmic abnormalities including optic neuropathy and/or optic neuritis, in some cases progressing to permanent blindness, papilledema, corneal degeneration, photosensitivity, eye discomfort, scotoma, lens opacities and macular degeneration have been reported (see "WARNINGS").

Asymptomatic corneal microdeposits are present in virtually all adult patients who have been on drug for more than 6 months. Some patients develop eye symptoms of halos, photophobia and dry eyes. Vision is rarely affected and drug discontinuation is rarely needed.

Dermatological adverse reactions occur in about 15% of patients, with photosensitivity being most common (about 10%). Sunscreen and protection from sun exposure may be helpful, and drug discontinuation is not usually necessary. Prolonged exposure to amiodarone occasionally results in a blue-gray pigmentation. This is slowly and occasionally incompletely reversible on discontinuation of drug but is of cosmetic importance only.

Cardiovascular adverse reactions, other than exacerbation of the arrhythmias, include the uncommon occurrence of congestive heart failure (3%) and bradycardia. Bradycardia usually responds to dosage reduction but may require a pacemaker for control. CHF rarely requires drug discontinuation. Cardiac conduction abnormalities occur infrequently and are reversible on discontinuation of drug.

The following side-effect rates are based on a retrospective study of 241 patients treated for 2 to 1,515 days (mean 441.3 days).

The following side effects were each reported in 10 to 33% of patients:

Gastrointestinal: Nausea and vomiting.

The following side effects were each reported in 4 to 9% of patients:

Dermatologic: Solar dermatitis/photosensitivity.
Neurologic: Malaise and fatigue, tremor/abnormal involuntary movements, lack of coordination, abnormal gait/ataxia, dizziness, paresthesias.
Gastrointestinal: Constipation, anorexia.
Ophthalmologic: Visual disturbances.
Hepatic: Abnormal liver-function tests.
Respiratory: Pulmonary inflammation or fibrosis.

The following side effects were each reported in 1 to 3% of patients:

Thyroid: Hypothyroidism, hyperthyroidism.
Neurologic: Decreased libido, insomnia, headache, sleep disturbances.
Cardiovascular: Congestive heart failure, cardiac arrhythmias, SA node dysfunction.
Gastrointestinal: Abdominal pain.
Hepatic: Nonspecific hepatic disorders.
Other: Flushing, abnormal taste and smell, edema, abnormal salivation, coagulation abnormalities.

The following side effects were each reported in less than 1% of patients:

Blue skin discoloration, rash, spontaneous ecchymosis, alopecia, hypotension and cardiac conduction abnormalities.

In surveys of almost 5,000 patients treated in open U.S. studies and in published reports of treatment with amiodarone HCl, the adverse reactions most frequently requiring discontinuation of amiodarone included pulmonary infiltrates or fibrosis, paroxysmal ventricular tachycardia, congestive heart failure and elevation of liver enzymes. Other symptoms causing discontinuations less often included visual disturbances, solar dermatitis, blue skin discoloration, hyperthyroidism and hypothyroidism.

Postmarketing Reports

In postmarketing surveillance, hypotension (sometimes fatal), sinus arrest, anaphylactic/anaphylactoid reaction (including shock), angioedema, urticaria, eosinophilic pneumonia, hepatitis, cholestatic hepatitis, cirrhosis, pancreatitis, renal impairment, renal insufficiency, acute renal failure, bronchospasm, possibly fatal respiratory disorders (including distress, failure, arrest, and ARDS), bronchiolitis obliterans organizing pneumonia (possibly fatal), fever, dyspnea, cough, hemoptysis, wheezing, hypoxia, pulmonary infiltrates and/or mass, pulmonary alveolar hemorrhage, pleural effusion, pleuritis, pseudotumor cerebri, parkinsonian symptoms such as akinesia and bradykinesia (sometimes reversible with discontinuation of therapy), syndrome of inappropriate antidiuretic hormone secretion (SIADH), thyroid nodules/thyroid cancer, toxic epidermal necrolysis (sometimes fatal), erythema multiforme, Stevens-Johnson syndrome, exfoliative dermatitis, drug rash with eosinophilia and systemic symptoms (DRESS), eczema, skin cancer, vasculitis, pruritus, hemolytic anemia, aplastic anemia, pancytopenia, neutropenia, thrombocytopenia, agranulocytosis, granuloma, myopathy, muscle weakness, rhabdomyolysis, demyelinating polyneuropathy, hallucination, confusional state, disorientation, delirium, epididymitis, and impotence, also have been reported with amiodarone therapy.

OVERDOSAGE

There have been cases, some fatal, of amiodarone HCl overdose.

In addition to general supportive measures, the patient's cardiac rhythm and blood pressure should be monitored, and if bradycardia ensues, a β-adrenergic agonist or a pacemaker may be used. Hypotension with inadequate tissue perfusion should be treated with positive inotropic and/or vasopressor agents. Neither amiodarone nor its metabolite is dialyzable.

The acute oral LD50 of amiodarone HCl in mice and rats is greater than 3,000 mg/kg.

DOSAGE AND ADMINISTRATION

BECAUSE OF THE UNIQUE PHARMACOKINETIC PROPERTIES, DIFFICULT DOSING SCHEDULE AND SEVERITY OF THE SIDE EFFECTS IF PATIENTS ARE IMPROPERLY MONITORED, PACERONE® TABLETS SHOULD BE ADMINISTERED ONLY BY PHYSICIANS WHO ARE EXPERIENCED IN THE TREATMENT OF LIFE-THREATENING ARRHYTHMIAS WHO ARE THOROUGHLY FAMILIAR WITH THE RISKS AND BENEFITS OF AMIODARONE THERAPY, AND WHO HAVE ACCESS TO LABORATORY FACILITIES CAPABLE OF ADEQUATELY MONITORING THE EFFECTIVENESS AND SIDE EFFECTS OF TREATMENT.

In order to insure that an antiarrhythmic effect will be observed without waiting several months, loading doses are required. A uniform, optimal dosage schedule for administration of Pacerone® Tablets has not been determined. Because of the food effect on absorption, Pacerone® Tablets should be administered consistently with regard to meals (see "CLINICAL PHARMACOLOGY"). Individual patient titration is suggested according to the following guidelines:

For life-threatening ventricular arrhythmias, such as ventricular fibrillation or hemodynamically unstable ventricular tachycardia: Close monitoring of the patients is indicated during the loading phase, particularly until risk of recurrent ventricular tachycardia or fibrillation has abated. Because of the serious nature of the arrhythmia and the lack of predictable time course of effect, loading should be performed in a hospital setting. Loading doses of 800 to 1,600 mg/day are required for 1 to 3 weeks (occasionally longer) until initial therapeutic response occurs. (Administration of Pacerone® Tablets in divided doses with meals is suggested for total daily doses of 1,000 mg or higher, or when gastrointestinal intolerance occurs.) If side effects become excessive, the dose should be reduced. Elimination of recurrence of ventricular fibrillation and tachycardia usually occurs within 1 to 3 weeks, along with reduction in complex and total ventricular ectopic beats.

Since grapefruit juice is known to inhibit CYP3A4-mediated metabolism of oral amiodarone in the intestinal mucosa, resulting in increased plasma levels of amiodarone, grapefruit juice should not be taken during treatment with oral amiodarone (see "PRECAUTIONS, Drug Interactions").

Upon starting Pacerone® Tablets therapy, an attempt should be made to gradually discontinue prior antiarrhythmic drugs (see section on "Drug Interactions"). When adequate arrhythmia control is achieved, or if side effects become prominent, Pacerone® Tablets dose should be reduced to 600 to 800 mg/day for one month and then to the maintenance dose, usually 400 mg/day (see "CLINICAL PHARMACOLOGY, Monitoring Effectiveness"). Some patients may require larger maintenance doses, up to 600 mg/day, and some can be controlled on lower doses. Pacerone® Tablets may be administered as a single daily dose, or in patients with severe gastrointestinal intolerance, as a b.i.d. dose. In each patient, the chronic maintenance dose should be determined according to antiarrhythmic effect as assessed by symptoms, Holter recordings and/or programmed electrical stimulation, and by patient tolerance. Plasma concentrations may be helpful in evaluating nonresponsiveness or unexpectedly severe toxicity (see "CLINICAL PHARMACOLOGY").

The lowest effective dose should be used to prevent the occurrence of side effects. In all instances, the physician must be guided by the severity of the individual patient's arrhythmia and response to therapy.

When dosage adjustments are necessary, the patient should be closely monitored for an extended period of time because of the long and variable half-life of amiodarone and the difficulty in predicting the time required to attain a new steady-state level of drug. Dosage suggestions are summarized below:

 | Loading Dose (Daily) | Adjustment and Maintenance Dose (Daily)
Ventricular Arrhythmias | 1 to 3 weeks | ~1 month | usual maintenance
 | 800 to 1,600 mg | 600 to 800 mg | 400 mg

HOW SUPPLIED

Repackaged by Aphena Pharma Solutions - TN.
See Repackaging Information for available configurations.

Pacerone® (Amiodarone HCl) Tablets, 100 mg, are available in bottles of 30 tablets (NDC 0245-0144-30), bottles of 100 tablets (NDC 0245-0144-11), and in unit dose cartons of 100 tablets (10 cards containing 10 tablets each) (NDC 0245-0144-01).

Pacerone® Tablets, 100 mg, are peach, round, flat-faced, uncoated tablets, debossed with "P" on one side, and "U-S" above "144" on the other side.

Pacerone® (Amiodarone HCl) Tablets, 200 mg, are available in bottles of 60 tablets (NDC 0245-0147-60), bottles of 90 tablets (NDC 0245-0147-90), bottles of 500 tablets (NDC 0245-0147-15) and in unit dose cartons of 100 tablets (10 cards containing 10 tablets each) (NDC 0245-0147-01).

Pacerone® Tablets, 200 mg, are pink, round, flat-faced, scored, uncoated tablets, debossed with "P200" on the unscored side, and "U-S" above and "0147" below the score on the reverse side.

STORAGE AND HANDLING

Store at 20-25°C (68-77°F). Excursions permitted to 15-30°C (59-86°F). [See USP Controlled Room Temperature.] Protect from light.

Dispense in a tight, light-resistant container with a child-resistant closure.

This product's label may have been revised after this insert was used in production. For further product information and current package insert, please visit www.pacerone.com or www.upsher-smith.com or call our professional services department toll-free at 1-800-654-2299

Medication Guide Pacerone® (PĀS-ər-ōn) Tablets (Amiodarone HCl)

Rx only

Read the Medication Guide that comes with Pacerone® Tablets before you start taking them and each time you get a refill. There may be new information. This Medication Guide does not take the place of talking with your doctor about your medical condition or your treatment.

What is the most important information I should know about Pacerone® Tablets?

Pacerone® Tablets can cause serious side effects that can lead to death including:

- lung damage
- liver damage
- worse heartbeat problems
- thyroid problems

Call your doctor or get medical help right away if you have any symptoms such as the following:

- shortness of breath, wheezing, or any other trouble breathing; coughing, chest pain, or spitting up of blood
- nausea or vomiting; passing brown or dark-colored urine; feel more tired than usual; your skin and whites of your eyes get yellow; or have stomach pain
- heart pounding, skipping a beat, beating very fast or very slowly; feel light-headed or faint
- weakness, weight loss or weight gain, heat or cold intolerance, hair thinning, sweating, changes in your menses, swelling of your neck (goiter), nervousness, irritability, restlessness, decreased concentration, depression in the elderly, or tremor.

Because of these possible side effects, Pacerone® Tablets should only be used in adults with life-threatening heartbeat problems called ventricular arrhythmias, for which other treatments did not work or were not tolerated.

Pacerone® Tablets can cause other serious side effects. See "What are the possible or reasonably likely side effects of Pacerone® Tablets?" for more information.

If you get serious side effects during treatment with Pacerone® Tablets you may need to stop Pacerone® Tablets, have your dose changed, or get medical treatment. Talk with your doctor before you stop taking Pacerone® Tablets.

You may still have side effects after stopping Pacerone® Tablets because the medicine stays in your body months after treatment is stopped.

Tell all your healthcare providers that you take or took Pacerone® Tablets. This information is very important for other medical treatments or surgeries you may have.

What are Pacerone® Tablets?

Amiodarone is a medicine used in adults to treat life-threatening heartbeat problems called ventricular arrhythmias, for which other treatment did not work or was not tolerated. Pacerone® Tablets have not been shown to help people with life-threatening heartbeat problems live longer. Treatment with Pacerone® Tablets should be started in a hospital to monitor your condition. You should have regular check-ups, blood tests, chest x-rays, and eye exams before and during treatment with Pacerone® Tablets to check for serious side effects.

Pacerone® Tablets have not been studied in children.

Who should not take Pacerone® Tablets?

Do not take Pacerone® Tablets if you:

- have certain heart conditions (heart block, very slow heart rate, or slow heart rate with dizziness or lightheadedness)
- have an allergy to amiodarone, iodine, or any of the other ingredients in Pacerone® Tablets. See the end of this Medication Guide for a complete list of ingredients in Pacerone® Tablets.

What should I tell my doctor before starting Pacerone® Tablets?

Tell your doctor about all of your medical conditions including if you:

- have lung or breathing problems
- have liver problems
- have or had thyroid problems
- have blood pressure problems
- are pregnant or planning to become pregnant. Amiodarone can harm your unborn baby. Amiodarone can stay in your body for months after treatment is stopped. Therefore, talk with your doctor before you plan to get pregnant.
- are breastfeeding. Amiodarone passes into your milk and can harm your baby. You should not breastfeed while taking Pacerone® Tablets. Also, amiodarone can stay in your body for months after treatment is stopped.

Tell your doctor about all the medicines you take including prescription and nonprescription medicines, vitamins and herbal supplements. Pacerone® Tablets and certain other medicines can interact with each other causing serious side effects. Sometimes the dose of Pacerone® Tablets or other medicines must be changed when they are used together. Especially, tell your doctor if you are taking:

- antibiotic medicines used to treat infections
- depression medicines
- blood thinner medicines
- HIV or AIDS medicines
- cimetidine (Tagamet®), a medicine for stomach ulcers or indigestion
- loratadine (for example: Claritin®, Alavert®), a medicine for allergy symptoms
- seizure medicines
- diabetes medicines
- cyclosporine, an immunosuppressive medicine
- dextromethorphan, a cough medicine
- medicines for your heart, circulation, or blood pressure
- water pills (diuretics)
- high cholesterol or bile medicines
- narcotic pain medicines
- St. John's Wort

Know the medicines you take. Keep a list of them with you at all times and show it to your doctor and pharmacist each time you get a new medicine. Do not take any new medicines while you are taking Pacerone® Tablets unless you have talked with your doctor.

How should I take Pacerone® Tablets?

- Take Pacerone® Tablets exactly as prescribed by your doctor.
- The dose of Pacerone® Tablets you take has been specially chosen for you by your doctor and may change during treatment. Keep taking your medicine until your doctor tells you to stop. Do not stop taking it because you feel better. Your condition may get worse. Talk with your doctor if you have side effects.
- Your doctor will tell you to take your dose of Pacerone® Tablets with or without meals. Make sure you take Pacerone® Tablets the same way each time.
- Do not drink grapefruit juice during treatment with Pacerone® Tablets. Grapefruit juice affects how amiodarone is absorbed in the stomach.
- Taking too many Pacerone® Tablets can be dangerous. If you take too many Pacerone® Tablets, call your doctor or go to the nearest hospital right away. You may need medical care right away.
- If you miss a dose, do not take a double dose to make up for the dose you missed. Continue with your next regularly scheduled dose.

What should I avoid while taking Pacerone® Tablets?

- Do not drink grapefruit juice during treatment with Pacerone® Tablets. Grapefruit juice affects how amiodarone is absorbed in the stomach.
- Avoid exposing your skin to the sun or sun lamps. Pacerone® Tablets can cause a photosensitive reaction. Wear sun-block cream or protective clothing when out in the sun.
- Avoid pregnancy during treatment with Pacerone® Tablets. Amiodarone can harm your unborn baby.
- Do not breastfeed while taking Pacerone® Tablets. Amiodarone passes into your milk and can harm your baby.

What are the possible or reasonably likely side effects of Pacerone® Tablets?

Pacerone® Tablets can cause serious side effects that lead to death including lung damage, liver damage, worse heartbeat problems and thyroid problems. See "What is the most important information I should know about Pacerone® Tablets?"

Some other serious side effects of Pacerone® Tablets include:

- vision problems that may lead to permanent blindness. You should have regular eye exams before and during treatment with Pacerone® Tablets. Call your doctor if you have blurred vision, see halos, or your eyes become sensitive to light.
- nerve problems. Pacerone® Tablets can cause a feeling of "pins and needles" or numbness in the hands, legs, or feet, muscle weakness, uncontrolled movements, poor coordination, and trouble walking.
- thyroid problems. Pacerone® Tablets can cause thyroid problems, including low thyroid function or overactive thyroid function. Your doctor may arrange regular blood tests to check your thyroid function during treatment with Pacerone® Tablets. Call your doctor if you have weakness, weight loss or weight gain, heat or cold intolerance, hair thinning, sweating, changes in your menses, swelling of your neck (goiter), nervousness, irritability, restlessness, decreased concentration, depression in the elderly, or tremor.
- skin problems. Pacerone® Tablets can cause your skin to be more sensitive to the sun or to turn a bluish-gray color. In most patients, skin color slowly returns to normal after stopping Pacerone® Tablets. In some patients, skin color does not return to normal.

Other side effects of Pacerone® Tablets include nausea, vomiting, constipation, and loss of appetite.

Call your doctor about any side effect that bothers you.

These are not all the side effects with Pacerone® Tablets. For more information, ask your doctor or pharmacist. You may report side effects to FDA at 1-800-FDA-1088. You may also report side effects to Upsher-Smith Laboratories at 1-888-650-3789.

How should I store Pacerone® Tablets?

- Store Pacerone® Tablets at room temperature. Protect from light. Keep Pacerone® Tablets in a tightly closed container.
- Safely dispose of Pacerone® Tablets that are out-of-date or no longer needed.
- Keep Pacerone® Tablets and all medicines out of the reach of children.

General information about Pacerone® Tablets

Medicines are sometimes prescribed for purposes other than those listed in a Medication Guide. Do not use Pacerone® Tablets for a condition for which it was not prescribed. Do not share Pacerone® Tablets with other people, even if they have the same symptoms that you have. It may harm them.

If you have any questions or concerns about Pacerone® Tablets, ask your doctor or healthcare provider. This Medication Guide summarizes the most important information about Pacerone® Tablets. If you would like more information, talk with your doctor. You can ask your doctor or pharmacist for information about Pacerone® Tablets that was written for healthcare professionals.

This Medication Guide may have been revised after this copy was produced. For more information and the most current Medication Guide, please visit www.pacerone.com or www.upsher-smith.com or call our professional services department toll-free at 1-800-654-2299.

What are the ingredients in Pacerone® Tablets?

Active Ingredient: amiodarone HCl, 100 mg and 200 mg

Inactive Ingredients: lactose monohydrate, magnesium stearate, povidone, pregelatinized corn starch, sodium starch glycolate, stearic acid, FD&C Red 40 (for 200 mg only) and FD&C Yellow 6.

This Medication Guide has been approved by the U.S. Food and Drug Administration.

Rx only

Manufactured by
UPSHER-SMITH LABORATORIES, INC.
Minneapolis, MN 55447

Tagamet is a registered trademark of SmithKline Beecham Pharmaceuticals Co.

Claritin is a registered trademark of Schering Corporation.

Alavert is a registered trademark of Wyeth.

R1111

Repackaging Information

Please reference the How Supplied section listed above for a description of individual tablets or capsules. This drug product has been received by Aphena Pharma - TN in a manufacturer or distributor packaged configuration and repackaged in full compliance with all applicable cGMP regulations. The package configurations available from Aphena are listed below:

Count | 200mg
30 | 67544-570-30

Store between 20°-25°C (68°-77°F). See USP Controlled Room Temperature. Dispense in a tight light-resistant container as defined by USP. Keep this and all drugs out of the reach of children.

Repackaged by:
Cookeville, TN 38506
20140509SC

PRINCIPAL DISPLAY PANEL - 200mg

NDC 67544-570 - Amiodarone HCI (Pacerone®) 200mg - Rx Only